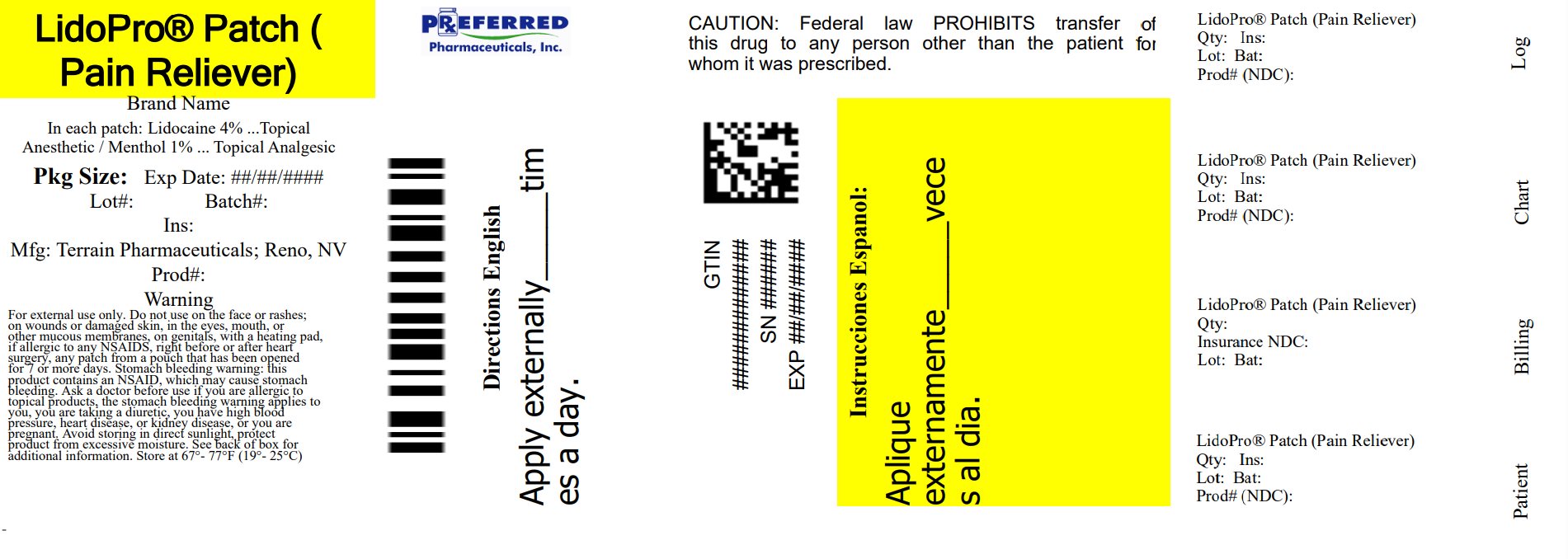 DRUG LABEL: LidoPro Patch
NDC: 68788-8630 | Form: PATCH
Manufacturer: Preferred Pharmaceuticals Inc.
Category: otc | Type: HUMAN OTC DRUG LABEL
Date: 20250716

ACTIVE INGREDIENTS: LIDOCAINE 4 mg/100 mg; MENTHOL, UNSPECIFIED FORM 1 mg/100 mg
INACTIVE INGREDIENTS: METHYLPARABEN; DIHYDROXYALUMINUM AMINOACETATE; GLYCERIN; SODIUM POLYACRYLATE (8000 MW); PROPYLENE GLYCOL; POLYSORBATE 80; WATER; TARTARIC ACID

LidoPro Patch

Active Ingredient

Lidocaine 4%

Purpose

Topical Anesthetic

Active Ingredient

Menthol 1%

Purpose

Topical Analgesic

Uses

For the temporary relief of pain.

Warnings

For external use only

Do not use

• on the face or rashes, on wounds or damaged skin

• in the eyes, mouth, or other mucous membranes

• on genitals

• with a heating pad

• right before or after heart surgery

• any patch from a pouch that has been opened for 7 or more days

• in large quantities, particularly over raw surfaces or blistered areas

• if tamper-evident seal is torn, broken, or missing

• more than 2 patches per day unless directed by a doctor

• children under 18 years of age

Ask a doctor before use if you have

• allergies to topical products

• high blood pressure, heart disease, or kidney disease.

When using this product

• avoid contact with eyes. If eye contact occurs, rinse thoroughly with water

• the risk of heart attack or stroke may increase if you use more than directed or for longer than directed.

Stop use and consult a doctor if

condition worsens, or if symptoms persist for more than 7 days or clear up and occur again within a few days.

If pregnant or breast feeding, ask a health professional before use.

Do not use during last 3 months of pregnancy because it may cause problems in the unborn child or complications during delivery.

Keep out of reach of children.

If put in mouth, seek medical help or contact a Poison Control Center right away. Dispose of the used patches by folding sticky ends together.

Directions

Adults 18 years and older:

• clean and dry affected area

• open pouch and remove one patch

• remove protective film from patch

• apply one patch to the affected area of pain and leave in place for 8 to 12 hours

• if pain lasts after using the first patch, a second patch may be applied for up to another 8 to 12 hours

• only use one patch at a time

• wash hands with soap and water after applying or removing patch

• reseal pouch containing unused patches after each use

Other information

• some individuals may not experience pain relief until several minutes or hours after applying the patch

• avoid storing product in direct sunlight

• protect product from excessive moisture

• store at 67-77°F (19-25°C)

Inactive Ingredients

dihydroxyaluminum aminoacetate, glycerol, methylparaben, polysorbate 80, propylene glycol, sodium polyacrylate, tartaric acid, water

Questions?

877-985-8377

Relabeled By: Preferred Pharmaceuticals Inc.